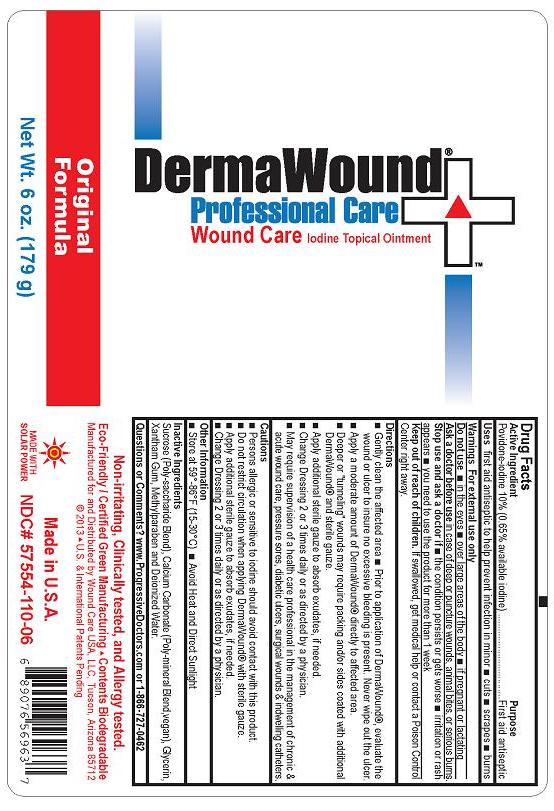 DRUG LABEL: DermaWound Wound Care
NDC: 57554-110 | Form: OINTMENT
Manufacturer: Progressive Doctors, LLC
Category: otc | Type: HUMAN OTC DRUG LABEL
Date: 20231215

ACTIVE INGREDIENTS: POVIDONE-IODINE 10 g/100 g
INACTIVE INGREDIENTS: SUCROSE; CALCIUM CARBONATE; GLYCERIN; XANTHAN GUM; METHYLPARABEN; WATER

DermaWound Wound Care Iodine Topical Ointment®

Active ingredient

Povidone-iodine 10% (0.65% available iodine)

Purpose

First aid antiseptic

Uses

first aid antiseptic to help prevent infection in minor

- cuts
- scrapes
- burns

Warnings

For external use only

Do not use

- in the eyes
- over large areas of the body
- if pregnant or lactating

Ask a doctor before use

in case of deep or puncture wounds, animal bites, or serious burns.

Stop use and ask a doctor if

- the condition persists or gets worse
- irritation or rash appears
- you need to use the product for more than 1 week

Keep Out of Reach of Children

If swallowed, get medical help or contact a Poison Control Center right away.

Directions

- Gently clean the affected area
- Prior to application of DermaWound , evaluate the wound or ulcer to insure no excessive bleeding is present. Never wipe out the ulcer.®
- Apply a moderate amount of DermaWound directly to affected area.®
- Deeper or "tunneling" wounds may require packing and/or sides coated with additional DermaWound and sterile gauze.®
- Apply additional sterile gauze to absorb exudates, if needed.
- Change Dressing 2 or 3 times daily or as directed by a physician.
- May require supervision of a health care professional in the management of chronic & acute wound care, pressure sores, diabetic ulcers, surgical wounds & indwelling catheters.

Cautions

- Persons allergic or sensitive to iodine should avoid contact with this product.
- Do not restrict circulation when applying DermaWound with sterile gauze.®
- Apply additional sterile gauze to absorb exudates, if needed.
- Change Dressing 2 or 3 times daily or as directed by a physician.

Other Information

- Store at 59°-86°F (15-30°C)
- Avoid Heat and Direct Sunlight

Inactive ingredients

Sucrose (Poly-saccharide Blend), Calcium Carbonate (Poly-mineral Blend, vegan), Glycerin, Xantham gum, Methylparaben and Deionized Water.

Questions or Comments?

www.ProgressiveDoctors.com or 1-866-727-0462

Non-irritating, Clinically tested, and Allergy tested.

Eco-Friendly / Certified Green Manufacturing Contents Biodegradable

Manufactured for and Distributed by Wound Care USA, LLC, Tucson, Arizona 85712

©2013 U.S. & International Patents Pending

Made in U.S.A.

Made With Solar Power

NDC# 57554-110-06

Package/Label Principal Display Panel

DermaWound Professional Care®

Wound Care Iodine Topical Ointment

Original Formula

Net Wt. 6 oz. (179 g)